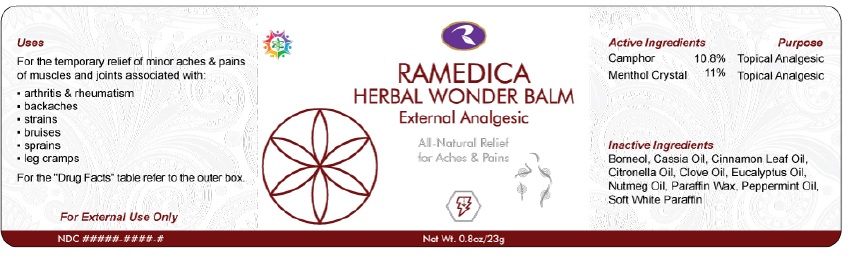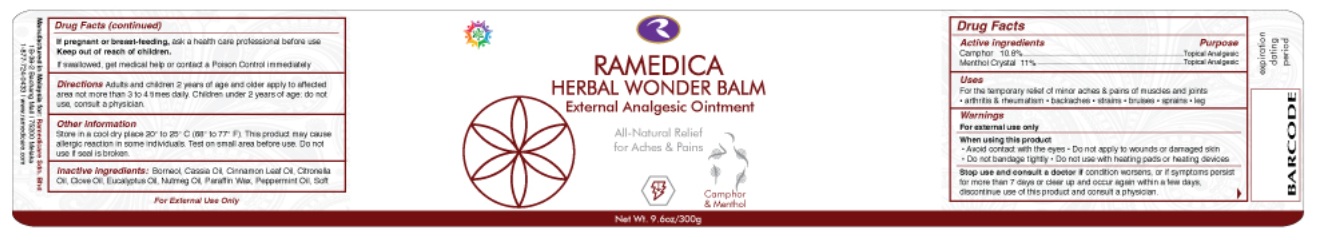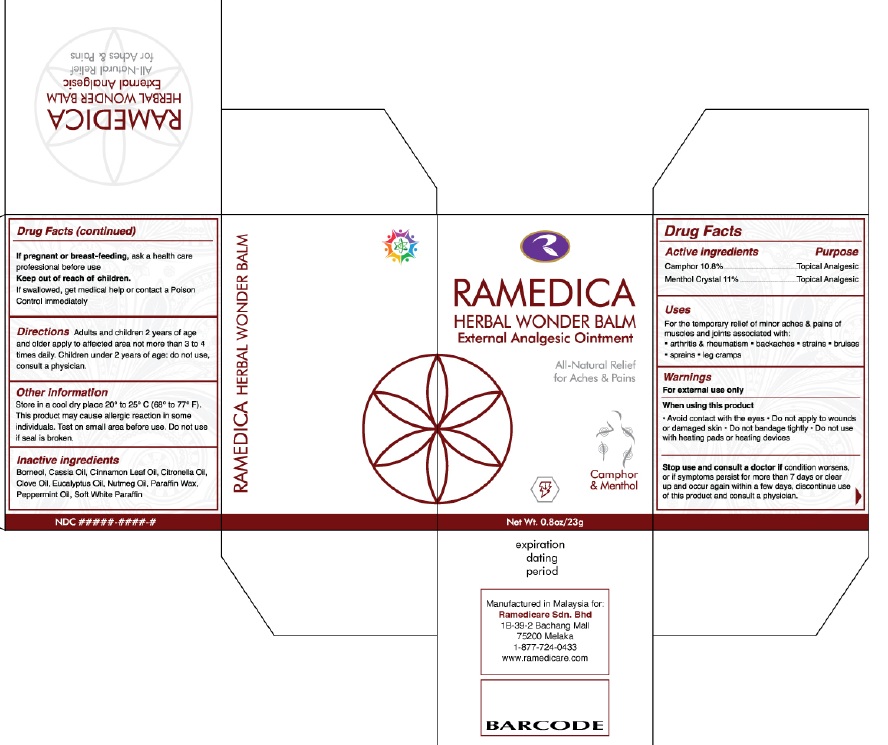 DRUG LABEL: Ramedica Herbal Wonder Balm
NDC: 66059-0005 | Form: OINTMENT
Manufacturer: Ramedicare Sdn. Bhd.
Category: otc | Type: HUMAN OTC DRUG LABEL
Date: 20250625

ACTIVE INGREDIENTS: CAMPHOR (NATURAL) 10.8 g/100 g; MENTHOL 11 g/100 g
INACTIVE INGREDIENTS: BORNEOL; CHINESE CINNAMON OIL; CINNAMON LEAF OIL; CITRONELLA OIL; CLOVE OIL; NUTMEG OIL; PARAFFIN; PEPPERMINT OIL; WHITE PETROLATUM; EUCALYPTUS OIL

Active Ingredients

Camphor 10.8%................................Topical Analgesic
Menthol Crystal 11%.........................Topical Analgesic

Uses

For the temporary relief of minor aches & pains of muscles and joints associated with:

- arthritis & rheumatism
- backaches
- strains
- bruises
- sprains
- leg cramps

Warnings

For external use only.

When using this product:

- Avoid contact with the eyes
- Do not apply to wounds or damaged skin
- Do not bandage tightly
- Do not use with heating pads or heating devices

Stop use and consult a doctor ifcondition worsens, or if symptoms persist for more than 7 days or clear up and occur again within a few days, discontinue use of this product and consult a physician.

If pregnant or breast-feeding, ask a health care professional before use

Keep out of reach of children.If swallowed, get medical help or contact a Poison Control immediately

Directions

- Adults and children 2 years of age and older apply to affected area not more than 3 to 4 times daily.
- Children under 2 years of age: do not use, consult a physician.

Other information

- Store in a cool dry place 20° to 25° C (68° to 77° F).
- This product may cause allergic reaction in some individuals.
- Test on small area before use. Do not use if seal is broken

Inactive Ingredients

Borneol, Cassia Oil, Cinnamon Leaf Oil, Citronella Oil, Clove Oil, Eucalyptus Oil, Nutmeg Oil, Paraffin Wax, Peppermint Oil, Soft White Paraffin